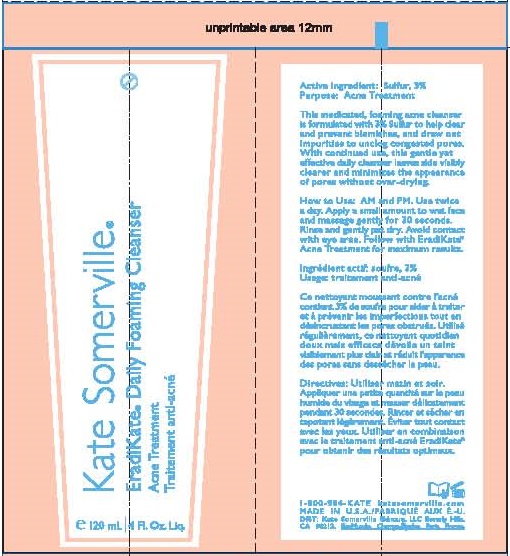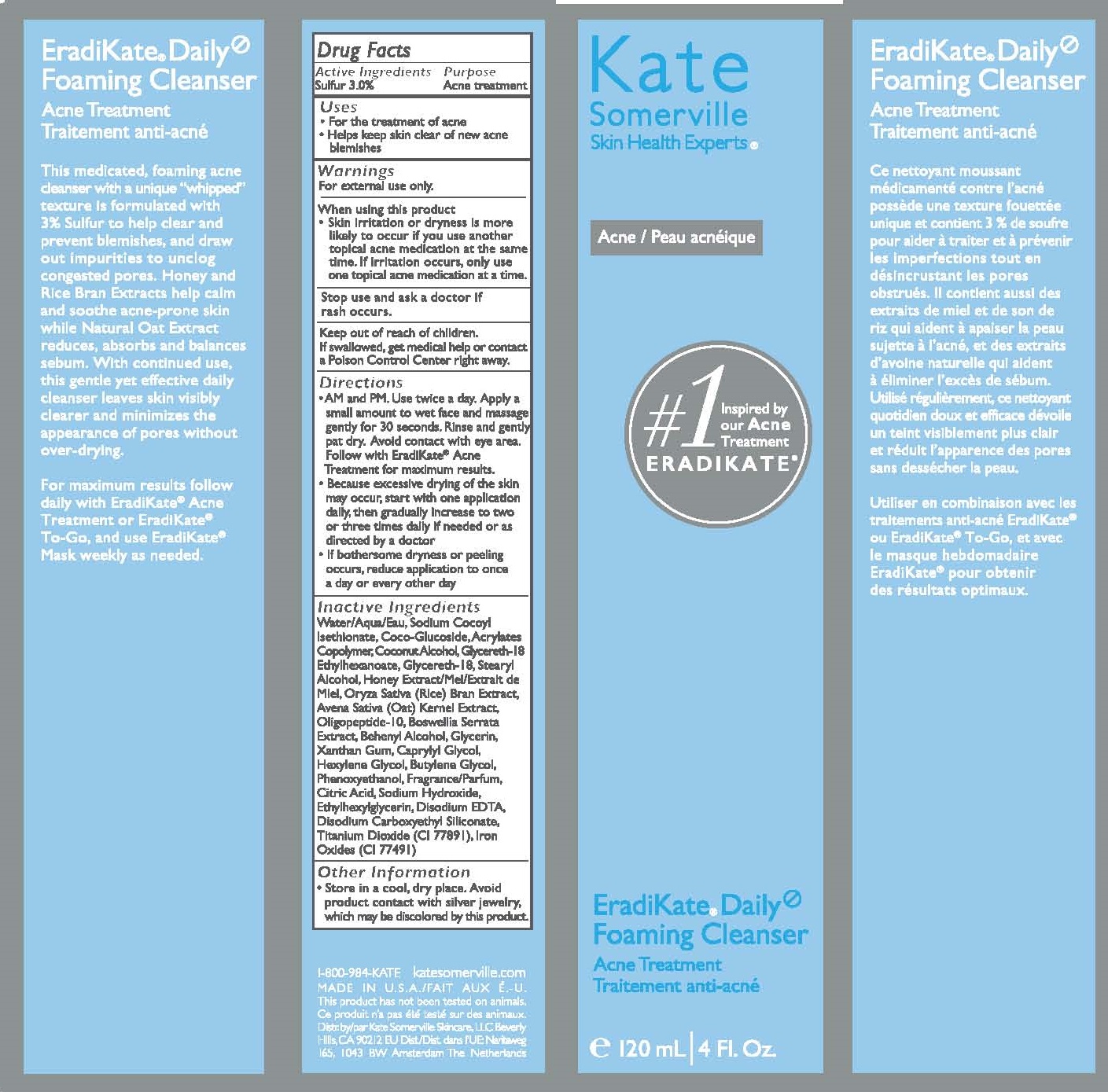 DRUG LABEL: EradiKate Daily Foaming Cleanser
NDC: 72204-902 | Form: GEL
Manufacturer: Rare Beauty Brands Inc.
Category: otc | Type: HUMAN OTC DRUG LABEL
Date: 20251201

ACTIVE INGREDIENTS: SULFUR 3 g/100 mL
INACTIVE INGREDIENTS: WATER; SODIUM COCOYL ISETHIONATE; COCO GLUCOSIDE; CARBOMER COPOLYMER TYPE A; COCONUT ALCOHOL; GLYCERETH-18 ETHYLHEXANOATE; GLYCERETH-18; STEARYL ALCOHOL; HONEY; ORYZA SATIVA WHOLE; AVENA SATIVA WHOLE; OLIGOPEPTIDE-10; BOSWELLIA SERRATA WHOLE; DOCOSANOL; GLYCERIN; XANTHAN GUM; CAPRYLYL GLYCOL; HEXYLENE GLYCOL; BUTYLENE GLYCOL; PHENOXYETHANOL; ANHYDROUS CITRIC ACID; SODIUM HYDROXIDE; ETHYLHEXYLGLYCERIN; EDETATE DISODIUM; DISODIUM CARBOXYETHYL SILICONATE; TITANIUM DIOXIDE; FERRIC OXIDE RED

Kate Somerville (as PLD) - EradiKate Daily Foaming Cleanser (43479-110)

ACTIVE INGREDIENT

SULFUR 3.0%

PURPOSE

ACNE TREATMENT

USES

- FOR THE TRETAMENT OF ACNE
- HELPS KEEP SKIN CLEAR OF NEW ACNE BLEMISHES

WARNINGS

FOR EXTERNAL USE ONLY

WHEN USING THIS PRODUCT

- SKIN IRRITATION OR DRYNESS IS MORE LIKELY TO OCCUR IF YOU USE ANOTHER TOPICAL ACNE MEDICATION AT THE SAME TIME. IF IRRITATION OCCURS, ONLY USE ONE TOPICAL ACNE MEDICATION AT A TIME.

STOP USE AND ASK A DOCTOR IF RASH OCCURS.

KEEP OUT OF REACH OF CHILDREN. IF SWALLOWED, GET MEDICAL HELP OR CONTACT A POISON CONTROL CENTER RIGHT AWAY.

DIRECTIONS

- AM AND PM. USE TWICE A DAY. APPLY A SMALL AMOUNT TO WET FACE AND MASSAGE GENTLY FOR 30 SECONDS. RINSE AND GENTLY PAT DRY. AVOID CONTACT WITH EYE AREA. FOLLOW WITH ERADIKATE ACNE TREATMENT FOR MAXIMUM RESULTS.
- BECAUSE EXCESSIVE DRYNESS OF THE SKIN MAY OCCUR, START WITH ONE APPLICATION DAILY, THEN GRADUALLY INCREASE TO TWO OR THREE TIMES DAILY IF NEEDED OR AS DIRECTED BY A DOCTOR.
- IF BOTHERSOME DRYNESS OR PEELING OCCURS, REDUCE APPLICATION TO ONCE A DAY OR EVERY OTHER DAY.

OTHER INFORMATION

- STORE IN A COOL, DRY PLACE. AVOID PRODUCT CONTACT WITH SILVER JEWELRY, WHICH MAY BE DISCOLORED BY THIS PRODUCT.

INACTIVE INGREDIENTS

WATER/AQUA/EAU, SODIUM COCOYL ISETHIONATE, COCO-GLUCOSIDE, ACRYLATES COPOLYMER, COCONUT ALCOHOL, GLYCERETH-18 ETHYLHEXANOATE, GLYCERETH-18, STEARYL ALCOHOL, HONEY EXTRACT/MEL/EXTRAIT DE MIEL, ORYZA SATIVA (OAT) KERNEL EXTRACT, OLIGOPEPTIDE-10, BOSWELLIA SERRATA EXTRACT, BEHENYL ALCOHOL, GLYCERIN, PHENOXYETHANOL, FRAGRANCE/PARFUM, CITRIC ACID, SODIUM HYDROXIDE, ETHYLHEXYLGLYCERIN, DISODIUM EDTA, DISODIUM CARBOXYETHYL SILICONATE, TITANIUM DIOXIDE (CI 77891), IRON OXIDES (CI 77491)